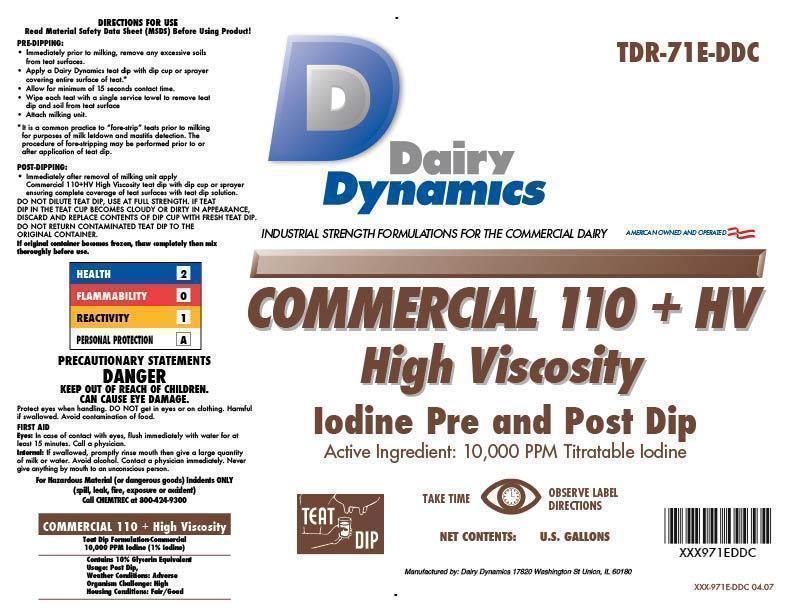 DRUG LABEL: COMMERCIAL 110 HV
NDC: 67351-971 | Form: SOLUTION
Manufacturer: Dairy Dynamics L.L.C.
Category: animal | Type: OTC ANIMAL DRUG LABEL
Date: 20141119

ACTIVE INGREDIENTS: IODINE 10 g/1 L

COMMERCIAL 110+HV

High Viscosity
Iodine Pre and Post Dip

Active Ingredient: 10,000 PPM Titratable Iodine

DIRECTIONS FOR USE

PRE-DIPPING

- Immediately prior to milking, remove any excessive soils from teat surfaces.
- Apply a Dairy Dynamics teat dip with dip cup or sprayer covering the entire surface of the teat.*
- Allow for a minimum 15 seconds contact time.
- Wipe each teat with a single service towel to remove teat dip and soil from teat surface.
- Attach milking unit.

* It is common practice to “fore-strip” teats prior to milking for the purposes of milk letdown and mastitis detection. The procedure of fore-stripping may be performed prior to or after application of teat dip.

POST-DIPPING

Immediately after removal of milking unit apply COMMERCIAL 110+HV High Viscosity with a dip cup or sprayer ensuring complete coverage of teat surfaces with teat dip solution.

DO NOT DILUTE TEAT DIP, USE AT FULL STRENGTH. IF TEAT DIP IN THE TEAT CUP BECOMES CLOUDY OR DIRTY IN APPEARANCE, DISCARD AND REPLACE CONTENTS IF THE DIP CUP WITH FRESH TEAT DIP. DO NOT RETURN CONTAMINATED TEAT DIP TO THE ORIGINAL CONTAINER.

If original container becomes frozen, thaw completely then mix thoroughly before use.

PRECAUTIONARY STATEMENTS

DANGER

KEEP OUT OF REACH OF CHILDREN.

CAN CAUSE EYE DAMAGE.

Protect eyes when handling. DO NOT get in eyes or on clothing. Harmful is swallowed. Avoid contamination of food.

FIRST AID

Eyes: In case of contact with eyes, flush immediately with plenty of water for at least 15 minutes. Call a physician.

Internal: If swallowed, promptly rinse mouth with water then give a large quantity of milk or water. Avoid alcohol. Contact a physician immediately. Never give anything by mouth to an unconscious person.

For Hazardous Material (or dangerous goods) Incidents ONLY (spill, leak, fire, exposure or accident)

Call CHEMTREC at 800-424-9300

HEALTH - 2

FLAMMABILITY - 0

REACTIVITY - 1

PERSONAL PROTECTION - A

INDICATIONS AND USAGE

Teat Dip Formulation - Commercial

10,000 PPM Iodine (1% Iodine)

Contains 10% Glycerin Equivalent

Usage: Post Dip

Weather Conditions: Adverse

Organism Challenge: High

Housing Conditions: Fair/Good

PRINCIPAL DISPLAY PANEL/REPRESENTATIVE LABEL

Dairy Dynamics

Industrial Strength Formulations for the Commercial Dairy

COMMERCIAL 110 + HV

High Viscosity

Iodine Pre and Post Dip

Active Ingredient: 10,000 PPM Titratable Iodine

TAKE TIME OBSERVE LABEL DIRECTIONS

NET CONTENTS: U.S. GALLONS

Manufactured by: Dairy Dynamics 17820 Washington St Union, IL 60180